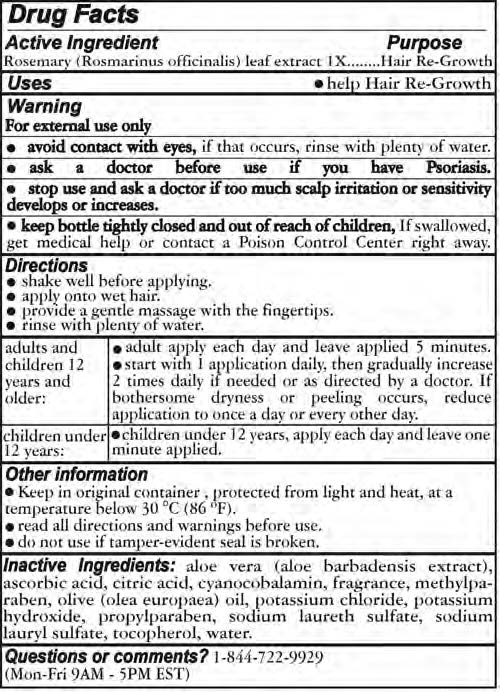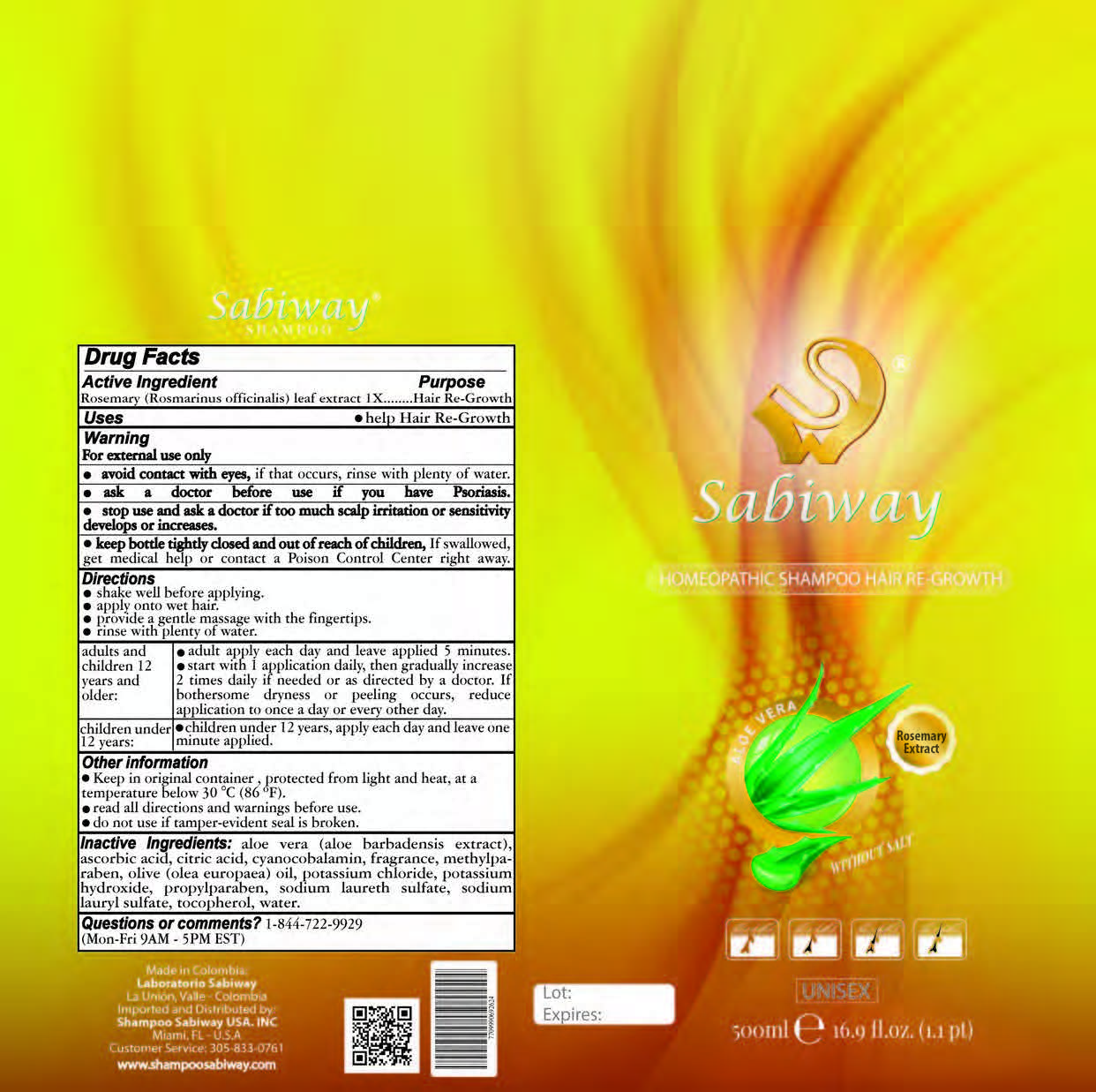 DRUG LABEL: Sabiway, Hair Re-Growth
NDC: 70527-001 | Form: SHAMPOO
Manufacturer: Navarrete Estacio Fernando
Category: homeopathic | Type: HUMAN OTC DRUG LABEL
Date: 20160309

ACTIVE INGREDIENTS: ROSEMARY 1 [hp_X]/10 mL
INACTIVE INGREDIENTS: CITRIC ACID MONOHYDRATE; TOCOPHEROL; METHYLPARABEN; OLIVE OIL; POTASSIUM CHLORIDE; ASCORBIC ACID; ALOE VERA LEAF; CYANOCOBALAMIN; POTASSIUM HYDROXIDE; PROPYLPARABEN; SODIUM LAURYL SULFATE; SODIUM LAURETH SULFATE; WATER

Active ingredient

Rosemary (Rosmarinus officinalis) leaf extract, 1X

Purpose

Hair Re-Growth

Keep out of reach of children

- Keep bottle tightly closed and out of reach of childeren, If swallowed, get medical help or contact a Poison Control Center right away.

Uses

- Help Hair Re-Growth

Warnings

For external use only

- avoid contact with eyes, if that occures, rinse with plenty of water
- ask a doctor before use if ou have Psoriasis
- stop use and ask a doctor if too much scalp irritation or sensitivity develops or increases

Directions

- Shake well before applying
- apply onto wet hair
- provide a gentle massage with teh fingertips
- rinse with plenty of water

Adults and Childrebn 12 years and older

- adult apply each day and leave applied 5 minutes
- start with 1 application daily, then gradually increase 2 times daily if needed or as directed by a doctor. If bothersome dryness or peeling occurs, reduce application to once a day or every other day

Children under 12 years

- Children under 12 years, apply each day and leave one minute applied

Inactive Ingredients

Aloe vera (aloe barbadensis extract), ascorbic acid, citric acid, cyanocobalamin, fragrance, methylparaben, olive (olea europaea) oil, potassium chloride, potassium hydroxide, propylparaben, sodium laureth sulfate, sodium lauryl sulfate, tocopherol, water